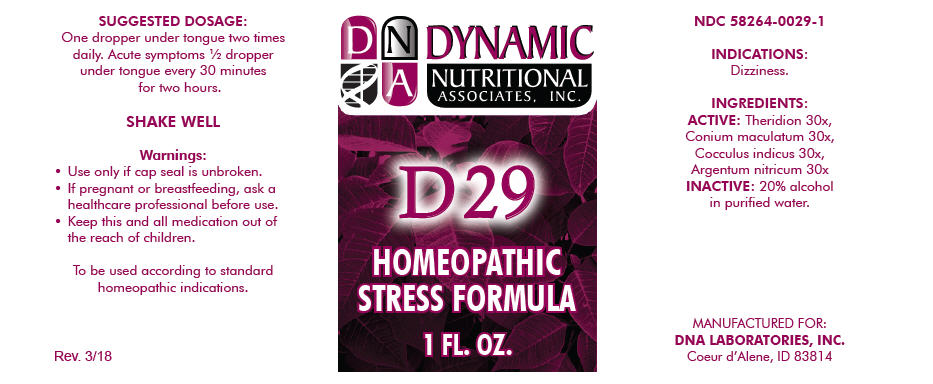 DRUG LABEL: D-29
NDC: 58264-0029 | Form: SOLUTION/ DROPS
Manufacturer: DNA Labs, Inc.
Category: homeopathic | Type: HUMAN OTC DRUG LABEL
Date: 20250113

ACTIVE INGREDIENTS: THERIDION CURASSAVICUM 30 [hp_X]/1 mL; CONIUM MACULATUM FLOWERING TOP 30 [hp_X]/1 mL; ANAMIRTA COCCULUS SEED 30 [hp_X]/1 mL; SILVER NITRATE 30 [hp_X]/1 mL
INACTIVE INGREDIENTS: ALCOHOL; WATER

D-29

NDC 58264-0029-1

INDICATIONS

PURPOSE

Dizziness.

INGREDIENTS

ACTIVE

Theridion 30x, Conium maculatum 30x, Cocculus indicus 30x, Argentum nitricum 30x

INACTIVE

20% alcohol in purified water.

SUGGESTED DOSAGE

One dropper under tongue two times daily. Acute symptoms ½ dropper under tongue every 30 minutes for two hours.

STORAGE AND HANDLING

SHAKE WELL

Warnings

- Use only if cap seal is unbroken.

PREGNANCY OR BREAST FEEDING

- If pregnant or breastfeeding, ask a healthcare professional before use.

KEEP OUT OF REACH OF CHILDREN

- Keep this and all medication out of the reach of children.

To be used according to standard homeopathic indications.

PRINCIPAL DISPLAY PANEL - 1 FL. OZ. Bottle Label

DYNAMIC
NUTRITIONAL
ASSOCIATES, INC.

D 29

HOMEOPATHIC
STRESS FORMULA

1 FL. OZ.